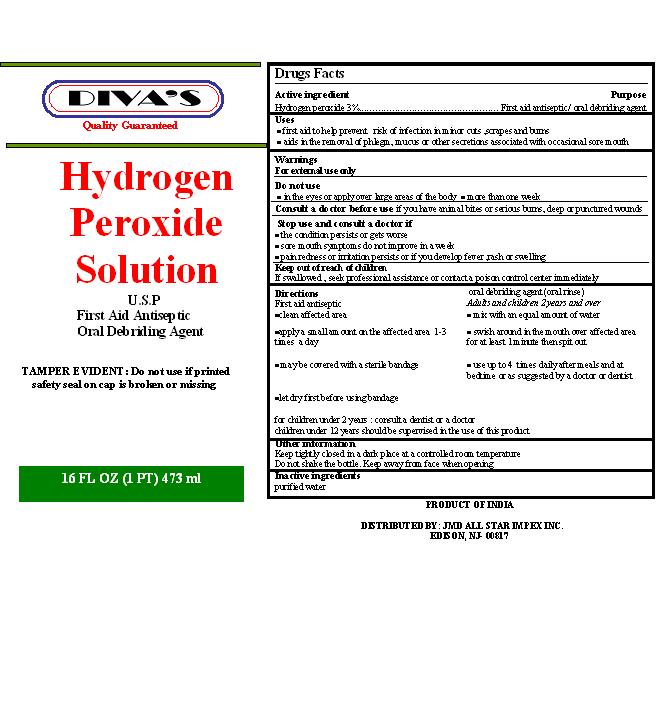 DRUG LABEL: Divas
NDC: 51444-004 | Form: LIQUID
Manufacturer: JMD All Star Impex Inc
Category: otc | Type: HUMAN OTC DRUG LABEL
Date: 20100708

ACTIVE INGREDIENTS: HYDROGEN PEROXIDE 3 mL/100 mL
INACTIVE INGREDIENTS: WATER

Drug Facts

Active Ingredient
Hydrogen peroxide 3%

Purpose
First aid antiseptic/oral debriding agent

Uses
• first aid to help prevent risk of infection in minor cuts ,scrapes and burns
• aids in the removal of phlegm, mucus or other secretions associated with occasional sore mouth

Warnings
For external use only
Do not use
• in the eyes or apply over large areas of the body • more than one week

Consult a doctor before use if you have
animal bites or serious burns, deep or punctured wounds

Stop use and consult a doctor if
• the condition persists or gets worse
• sore mouth symptoms do not improve in a week
• pain redness or irritation persists or if you develop fever ,rash or swelling

Keep out of reach of children
In case of an accidental ingestion, seek professional assistance or contact a poison control center immediately

Directions
First aid antiseptic oral debriding agent (oral rinse)
•clean affected area Adults and children 2 years and over
•apply a small amount of this product on the affected area 1-3 times a day • mix with an equal amount of water
• may be covered with a sterile bandage • swish around in the mouth over affected area for at least 1 minute then spit out
• use up to 4 times daily after meals and at
bedtime or as suggested by a doctor or dentist
•let dry first before using bandage
for children under 2 years: consult a dentist or a doctor
children under 12 years should be supervised in the use of this product

Other information
Keep tightly closed in a dark place at a controlled room temperature
Do not shake the bottle. Keep away from face when opening

Inactive ingredients
purified water

Package Label